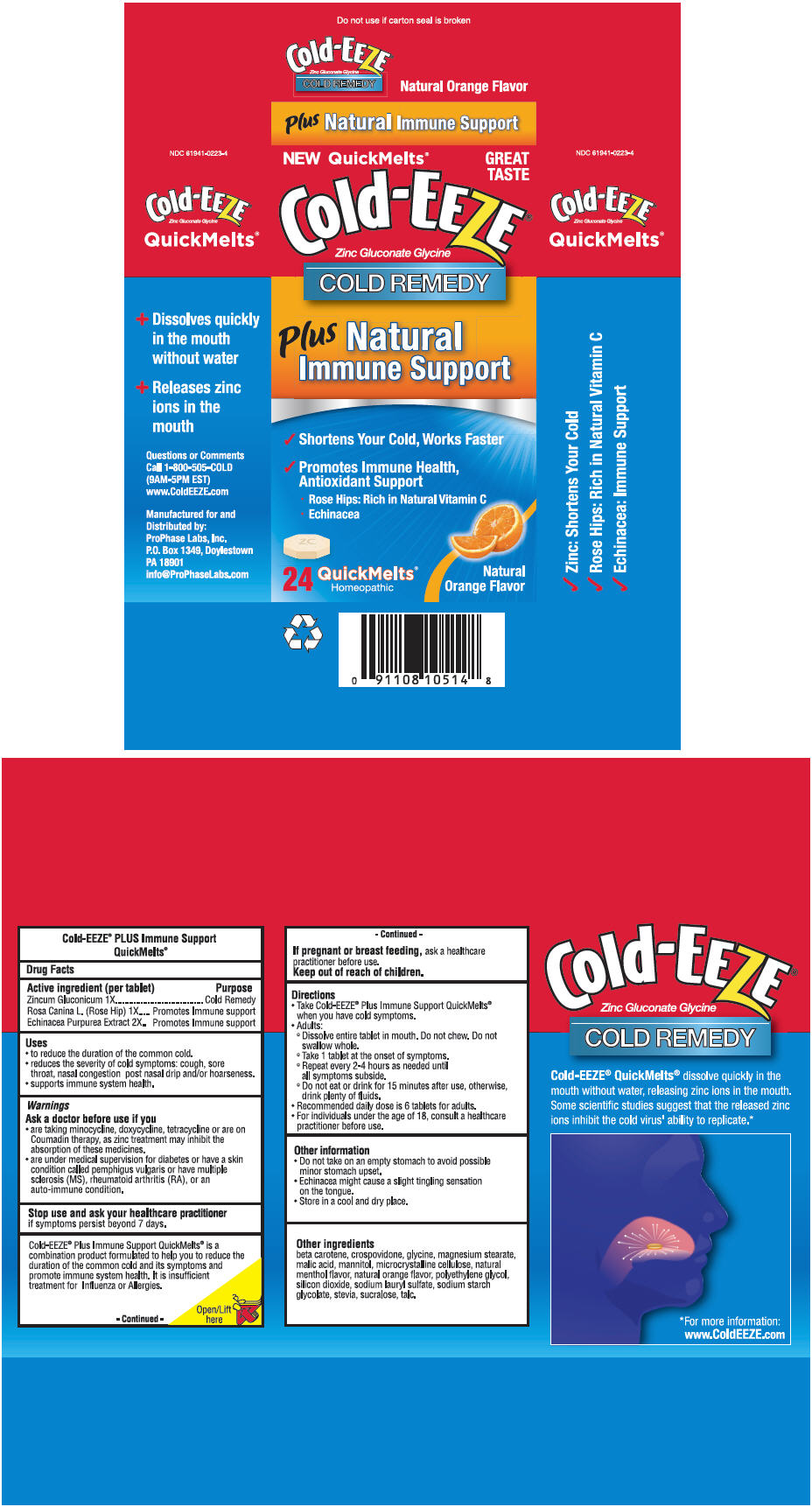 DRUG LABEL: Cold-EEZE 
NDC: 61941-0223 | Form: TABLET, ORALLY DISINTEGRATING
Manufacturer: ProPhase Labs, Inc.
Category: homeopathic | Type: HUMAN OTC DRUG LABEL
Date: 20130822

ACTIVE INGREDIENTS: Zinc Gluconate 1 [hp_X]/1 1; ROSA CANINA LEAF 1 [hp_X]/1 1; ECHINACEA PURPUREA 2 [hp_X]/1 1
INACTIVE INGREDIENTS: GLYCINE; .BETA.-CAROTENE; CROSPOVIDONE; MAGNESIUM STEARATE; MALIC ACID; MANNITOL; CELLULOSE, MICROCRYSTALLINE; MENTHOL; ORANGE; POLYETHYLENE GLYCOLS; SILICON DIOXIDE; SODIUM LAURYL SULFATE; SODIUM STARCH GLYCOLATE TYPE A POTATO; STEVIA REBAUDIUNA LEAF; SUCRALOSE; TALC

Cold-EEZE®
PLUS Immune Support

Drug Facts

ACTIVE INGREDIENT

Active ingredient (per tablet) | Purpose
Zincum Gluconicum 1X | Cold Remedy
Rosa Canina L. (Rose Hip) 1X | Promotes Immune support
Echinacea Purpurea Extract 2X | Promotes Immune support

Uses

- to reduce the duration of the common cold.
- reduces the severity of cold symptoms: cough, sore throat, nasal congestion post nasal drip and/or hoarseness.
- supports immune system health.

Warnings

Ask a doctor before use if you

- are taking minocycline, doxycycline, tetracycline or are on Coumadin therapy, as zinc treatment may inhibit the absorption of these medicines.
- are under medical supervision for diabetes or have a skin condition called pemphigus vulgaris or have multiple sclerosis (MS), rheumatoid arthritis (RA), or an auto-immune condition.

Stop use and ask your healthcare practitioner if symptoms persist beyond 7 days.

DO NOT USE

Cold-EEZE® Plus Immune Support QuickMelts® is a combination product formulated to help you to reduce the duration of the common cold and its symptoms and promote immune system health. It is insufficient treatment for Influenza or Allergies.

PREGNANCY OR BREAST FEEDING

If pregnant or breast feeding, ask a healthcare practitioner before use.

Keep out of reach of children.

Directions

- Take Cold-EEZE® Plus Immune Support QuickMelts® when you have cold symptoms.
- Adults:
  - Dissolve entire tablet in mouth. Do not chew. Do not swallow whole.
  - Take 1 tablet at the onset of symptoms.
  - Repeat every 2-4 hours as needed until all symptoms subside.
  - Do not eat or drink for 15 minutes after use, otherwise, drink plenty of fluids.
- Recommended daily dose is 6 tablets for adults.
- For individuals under the age of 18, consult a healthcare practitioner before use.

Other information

- Do not take on an empty stomach to avoid possible minor stomach upset.
- Echinacea might cause a slight tingling sensation on the tongue.
- Store in a cool and dry place.

Other ingredients

beta carotene, crospovidone, glycine, magnesium stearate, malic acid, mannitol, microcrystalline cellulose, natural menthol flavor, natural orange flavor, polyethylene glycol, silicon dioxide, sodium lauryl sulfate sodium starch glycolate, stevia, sucralose, talc.

Distributed by:
ProPhase Labs, Inc.
P.O. Box 1349, Doylestown
PA 18901

PRINCIPAL DISPLAY PANEL - 24 Tablet Package

NEW QuickMelts®

GREAT
TASTE

Cold-EEZE®

Zinc Gluconate Glycine

COLD REMEDY

Plus Natural
Immune Support

✔ Shortens Your Cold, Works Faster
✔ Promotes Immune Health,
  Antioxidant Support
  - Rose Hips: Rich in Natural Vitamin C
  - Echinacea

24 QuickMelts®
Homeopathic

Natural
Orange Flavor